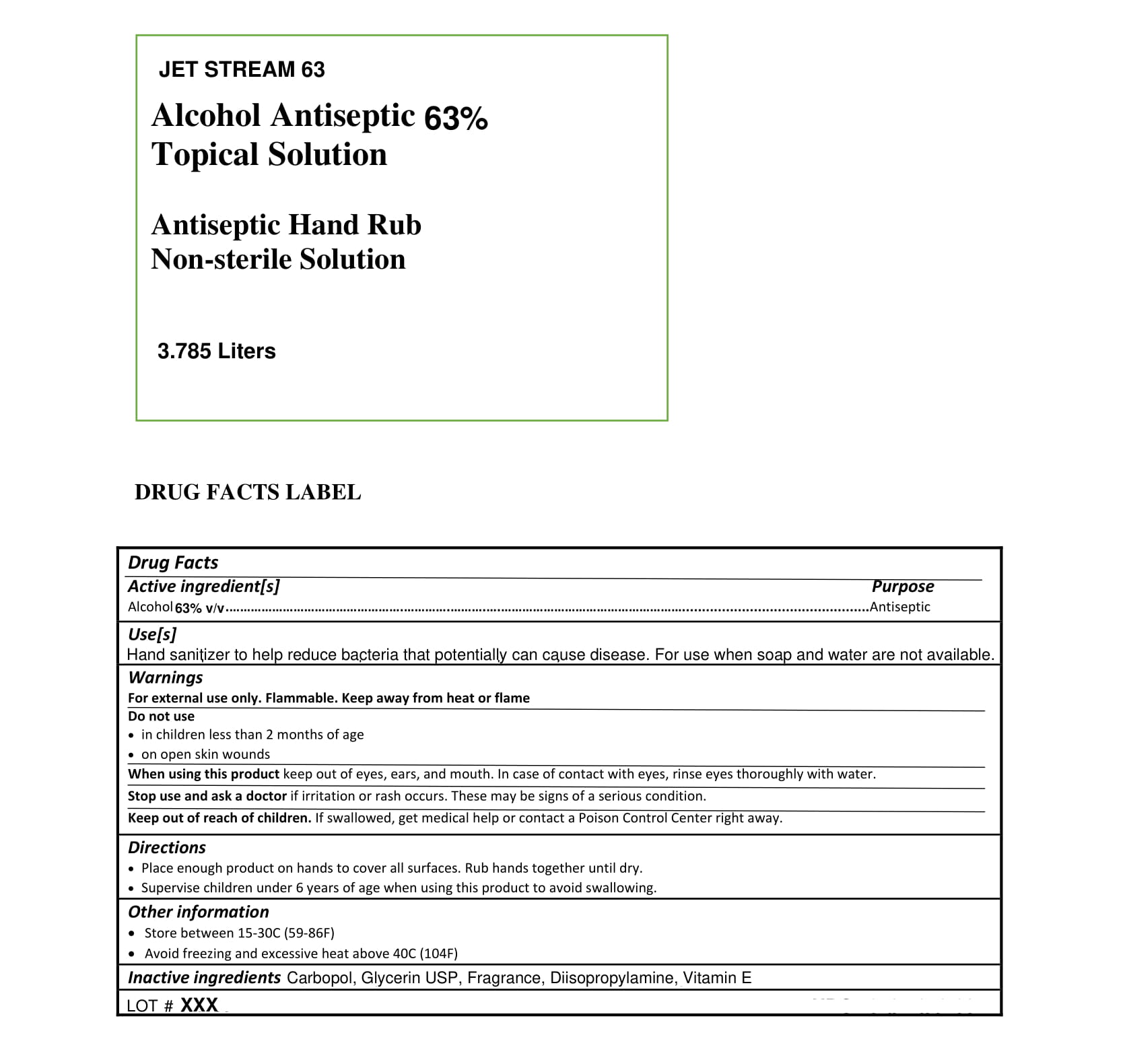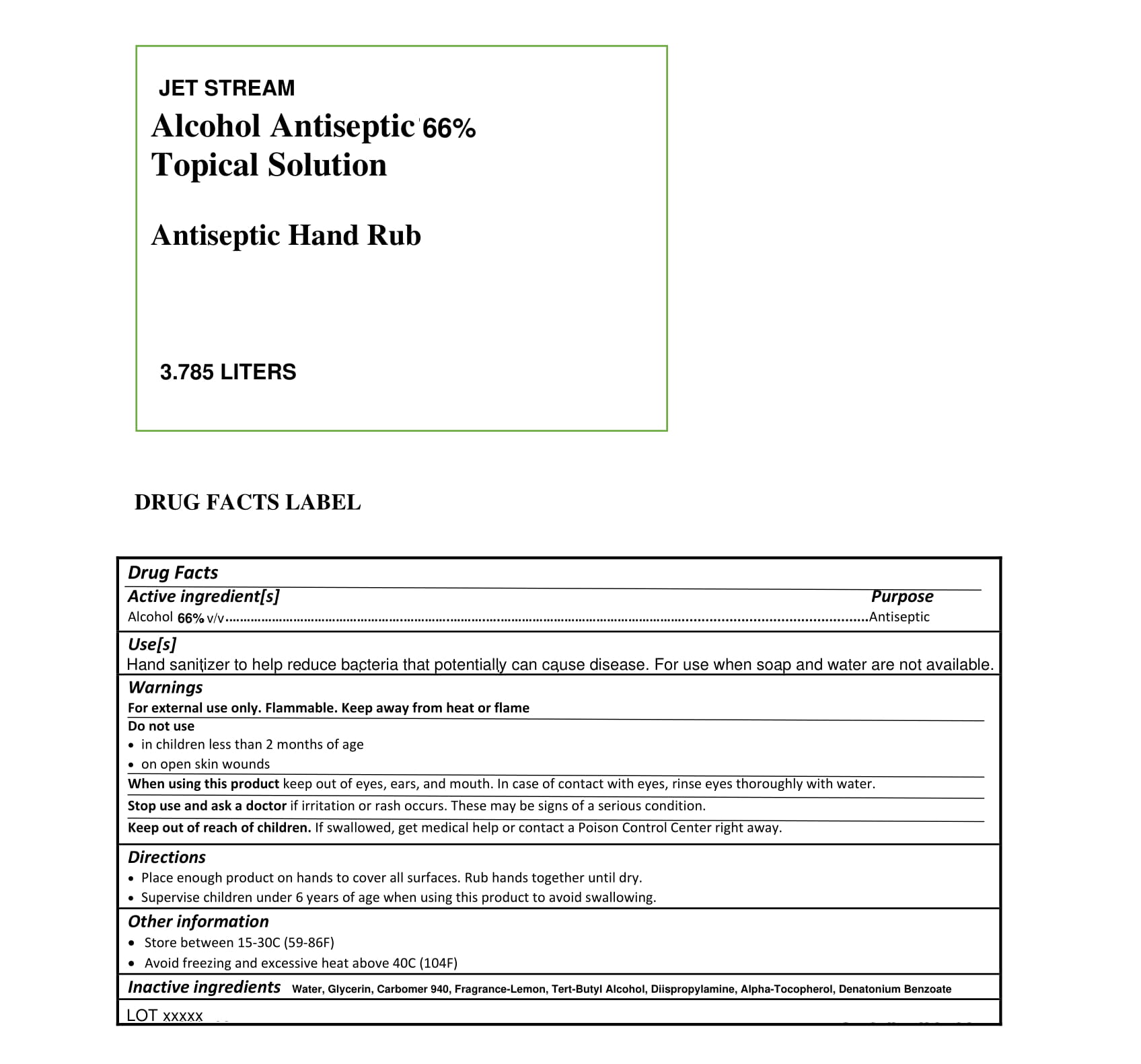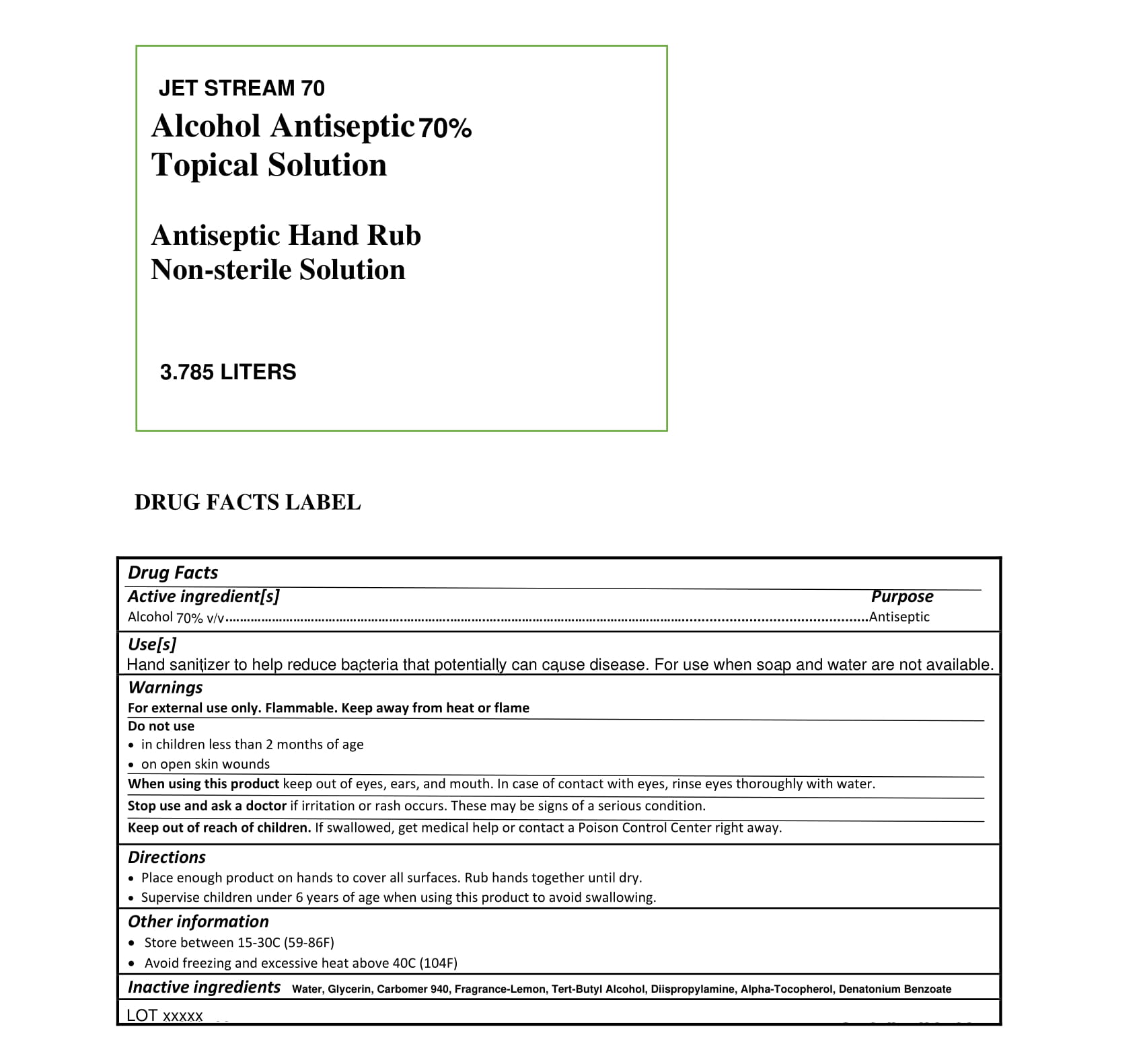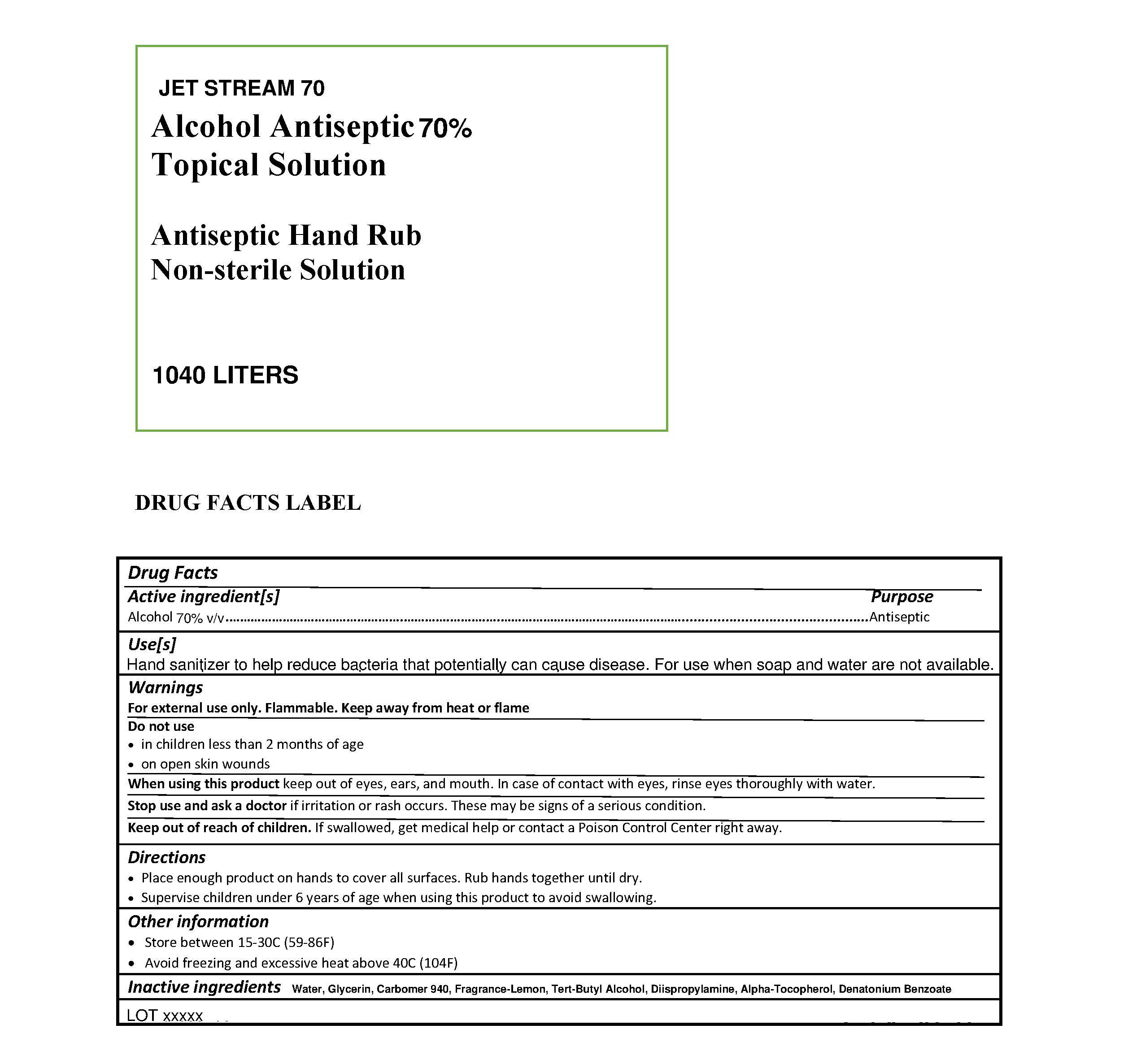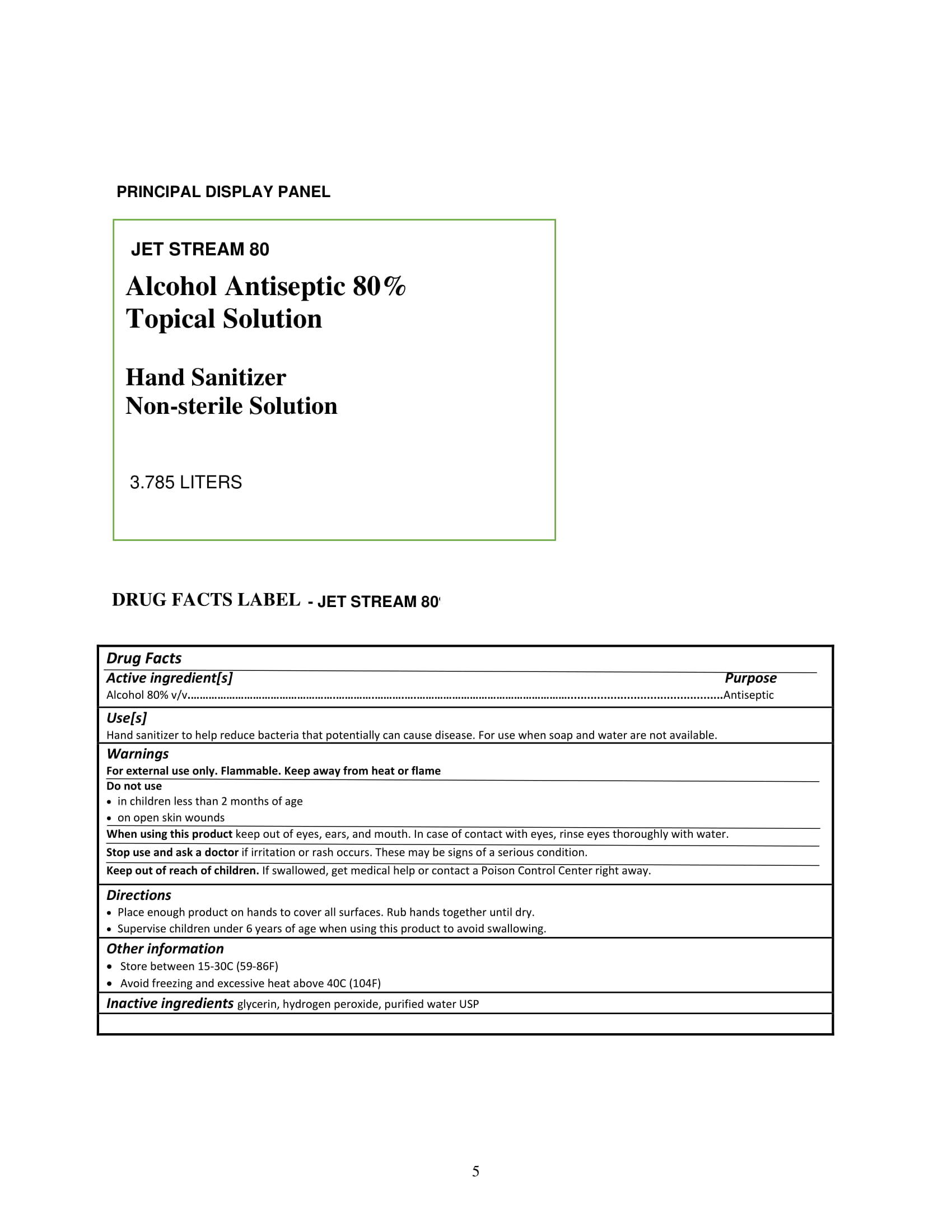 DRUG LABEL: Jet Stream 63
NDC: 73794-003 | Form: GEL
Manufacturer: JET STREAM FUELS, INC.
Category: otc | Type: HUMAN OTC DRUG LABEL
Date: 20201216

ACTIVE INGREDIENTS: ALCOHOL 63 mL/100 mL
INACTIVE INGREDIENTS: TERT-BUTYL ALCOHOL; GLYCERIN; .ALPHA.-TOCOPHEROL ACETATE; CARBOMER HOMOPOLYMER, UNSPECIFIED TYPE

Hand Sanitizer

Directions

• Place enough product on hands to cover all surfaces. Rub hands together until dry.
• Supervise children under 6 years of age when using this product to avoid swallowing.

Warnings

For external use only. Flammable. Keep away from heat or flame

PURPOSE

Antiseptic

.

Indications and Usage

Hand Sanitizer to reduce bacteria that can potentially cause disease. For use when soap and water are not available

Keep out of reach of children. If swallowed, get medical help or contact a Poison Control Center right away.

Inactive Ingredient Section

Water, Glycerin, Carbomer 940, Fragrance-Lemon, Tert-Butyl Alcohol, Diispropylamine, Alpha-Tocopherol, Denatonium Benzoate

Alcohol 80%v/v Purpose Antiseptic

NDC 73794-004-00 liter/gallon

70 ml NDC 73794-004-00

NDC 73794-003-00

63 ml NDC 73794-003-00

NDC 73794-005-00

66 ml NDC 73794-005-00

73794-012-00

80 ml NDC 73794-012-00